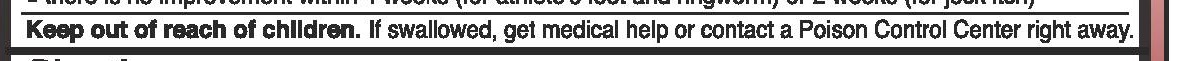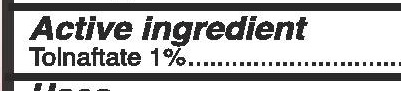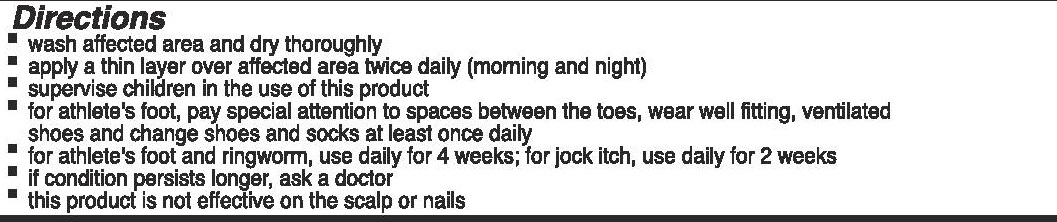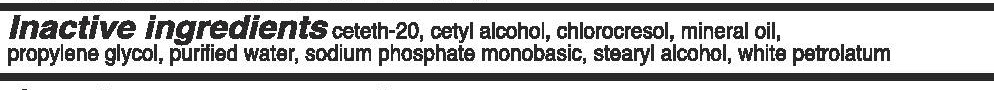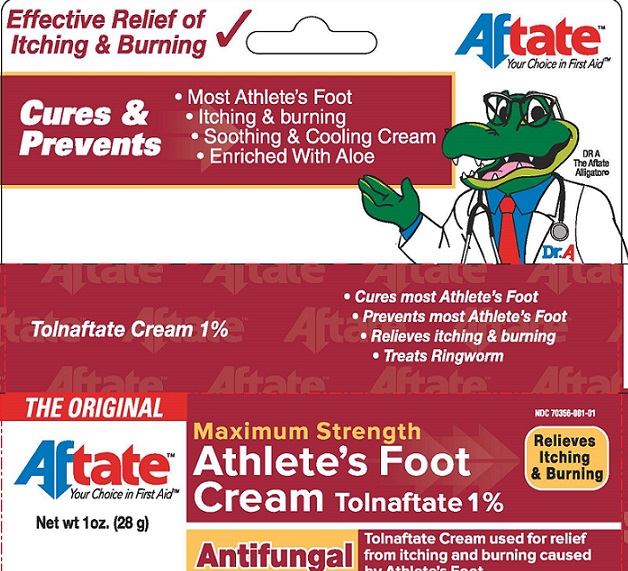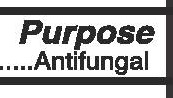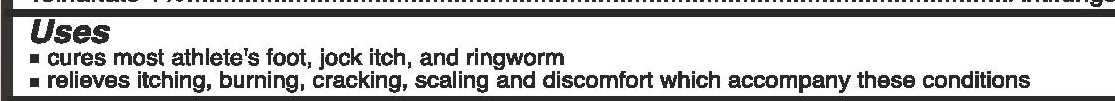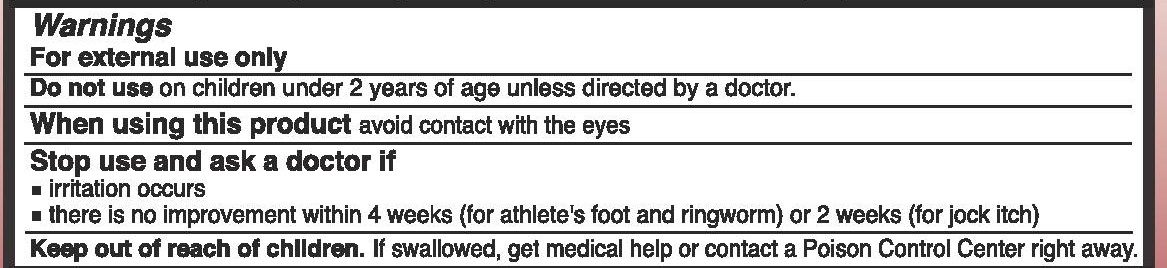 DRUG LABEL: Aftate Athlete Foot Cream
NDC: 70356-001 | Form: CREAM
Manufacturer: Sabel Med LLC
Category: otc | Type: HUMAN OTC DRUG LABEL
Date: 20161123

ACTIVE INGREDIENTS: TOLNAFTATE 1 g/100 g
INACTIVE INGREDIENTS: SODIUM PHOSPHATE, MONOBASIC, UNSPECIFIED FORM; CETYL ALCOHOL; MINERAL OIL; PROPYLENE GLYCOL 1-(2-METHYLBUTYRATE); PROPYLPARABEN; CHLOROCRESOL; CETETH-20; WATER; PETROLATUM

Aftate-Tolnaftate Athlete's Foot Cream- 1 oz and 0.5 oz